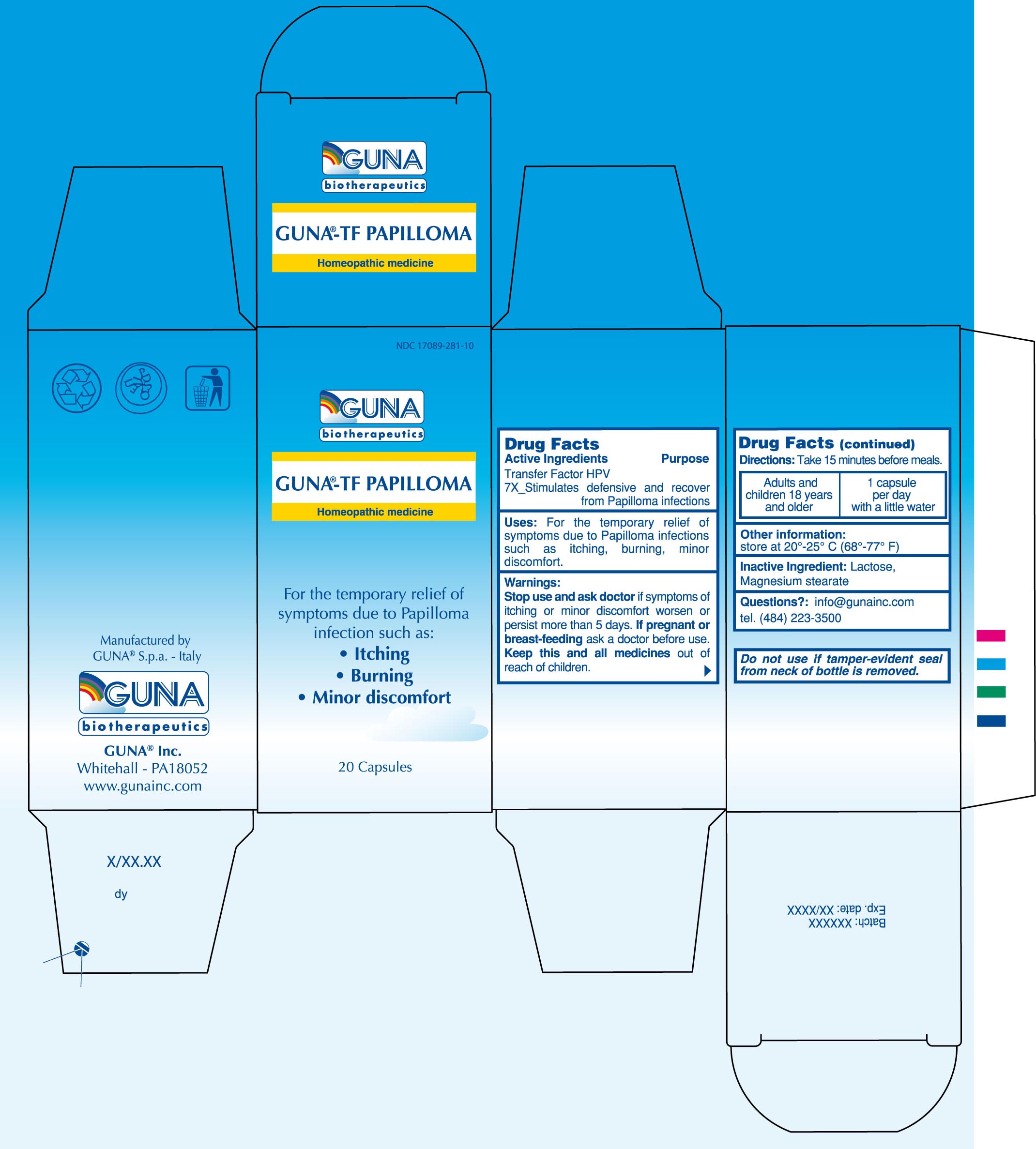 DRUG LABEL: GUNA-TF PAPILLOMA
NDC: 17089-281 | Form: CAPSULE, GELATIN COATED
Manufacturer: Guna spa
Category: homeopathic | Type: HUMAN OTC DRUG LABEL
Date: 20100331

ACTIVE INGREDIENTS: HUMAN PAPILLOMAVIRUS 7 [hp_X]/4600 mg
INACTIVE INGREDIENTS: LACTOSE 4048 mg/4600 mg; MAGNESIUM STEARATE 92 mg/4600 mg

DRUG FACTS

ACTIVE INGREDIENTS/PURPOSE

TRANSFER FACTOR HPV 7X STIMULATES DEFENSIVE AND RECOVER FROM PAPILLOMA INFECTIONS

USES

For the temporary relief of symptoms due to Papilloma infections such as: itching, burning, minor discomfort

WARNINGS

Stop use and ask doctor if symptoms of itching or minor discomfort worsen or persist more than 5 days

PREGNANCY

If pregnant or breast-feeding ask a doctor before use

WARNINGS

Keep this and all medicines out of reach of children

DIRECTIONS

Take 15 minutes before meals
Adults 18 years and older 1 capsule per day with a little water

QUESTIONS

Questions?: info@gunainc.com
Tel. (484) 223-3500